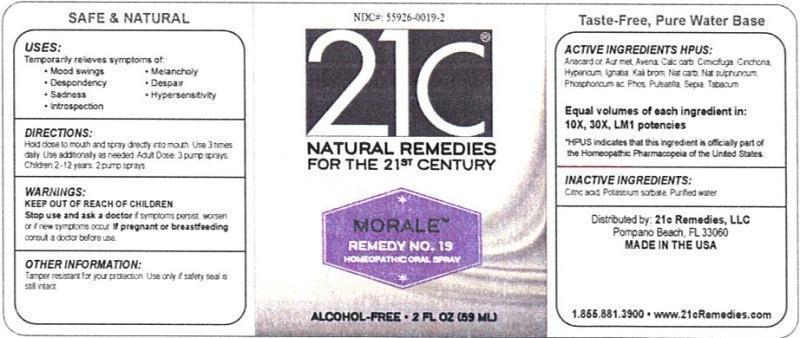 DRUG LABEL: Morale Remedy No. 19
NDC: 55926-0019 | Form: LIQUID
Manufacturer: Speer Laboratories, LLC
Category: homeopathic | Type: HUMAN OTC DRUG LABEL
Date: 20130730

ACTIVE INGREDIENTS: SEMECARPUS ANACARDIUM JUICE 10 [hp_X]/59 mL; GOLD 10 [hp_X]/59 mL; OYSTER SHELL CALCIUM CARBONATE, CRUDE 10 [hp_X]/59 mL; BLACK COHOSH 10 [hp_X]/59 mL; HYPERICUM PERFORATUM 10 [hp_X]/59 mL; STRYCHNOS IGNATII SEED 10 [hp_X]/59 mL; POTASSIUM BROMIDE 10 [hp_X]/59 mL; SODIUM CARBONATE 10 [hp_X]/59 mL; SODIUM SULFATE 10 [hp_X]/59 mL; PHOSPHORIC ACID 10 [hp_X]/59 mL; PHOSPHORUS 10 [hp_X]/59 mL; PULSATILLA VULGARIS 10 [hp_X]/59 mL; SEPIA OFFICINALIS JUICE 10 [hp_X]/59 mL; TOBACCO LEAF 10 [hp_X]/59 mL
INACTIVE INGREDIENTS: CITRIC ACID MONOHYDRATE; POTASSIUM SORBATE; WATER

Morale Remedy No. 19

ACTIVE INGREDIENT

Active Ingredients HPUS: Anacardium orientale, Aurum metallicum, Calcarea carbonica, Cimicifuga racemosa, Hypericum perforatum, Ignatia amara, Kale bromatum, Natrum carbonicum, Natrum sulphuricum, Phosphoricum acidum, Phosphorus, Pulsatilla, Sepia, Tabacum.

Equal volumes of each ingredient in: 10X, 30X, LM1 potencies

HPUS indicates that this ingredient is officially part of the Homeopathic Pharmacopeia of the United States.

Inactive Ingredients: Citric acid, Potassium sorbate, Purified water.

INDICATIONS AND USAGE

Uses: Temporarily relieves symptoms of:

- mood swings
- despondency
- sadness
- introspection
- melancholy
- despair
- Hypersensitivity

Directions:

Hold close to mouth and spray directly into mouth. Use 3 times daily. Use additionally as needed. Adult dose: 3 pump sprays. Children 2-12 years: 2 pump sprays.

Keep out of reach of children.

WARNINGS

Warnings: Stop use and ask a doctor if symptoms persist, worsen or if new symptoms occur. If pregnant or breastfeeding, consult a doctor before use.

OTHER SAFETY INFORMATION

Tamper resistant for your protection. Use only if safety seal is still intact.

PURPOSE

Uses: Temporarily relieves symptoms of: mood swings, despondency, sadness, introspection, melancholy, despair, Hypersensitivity.